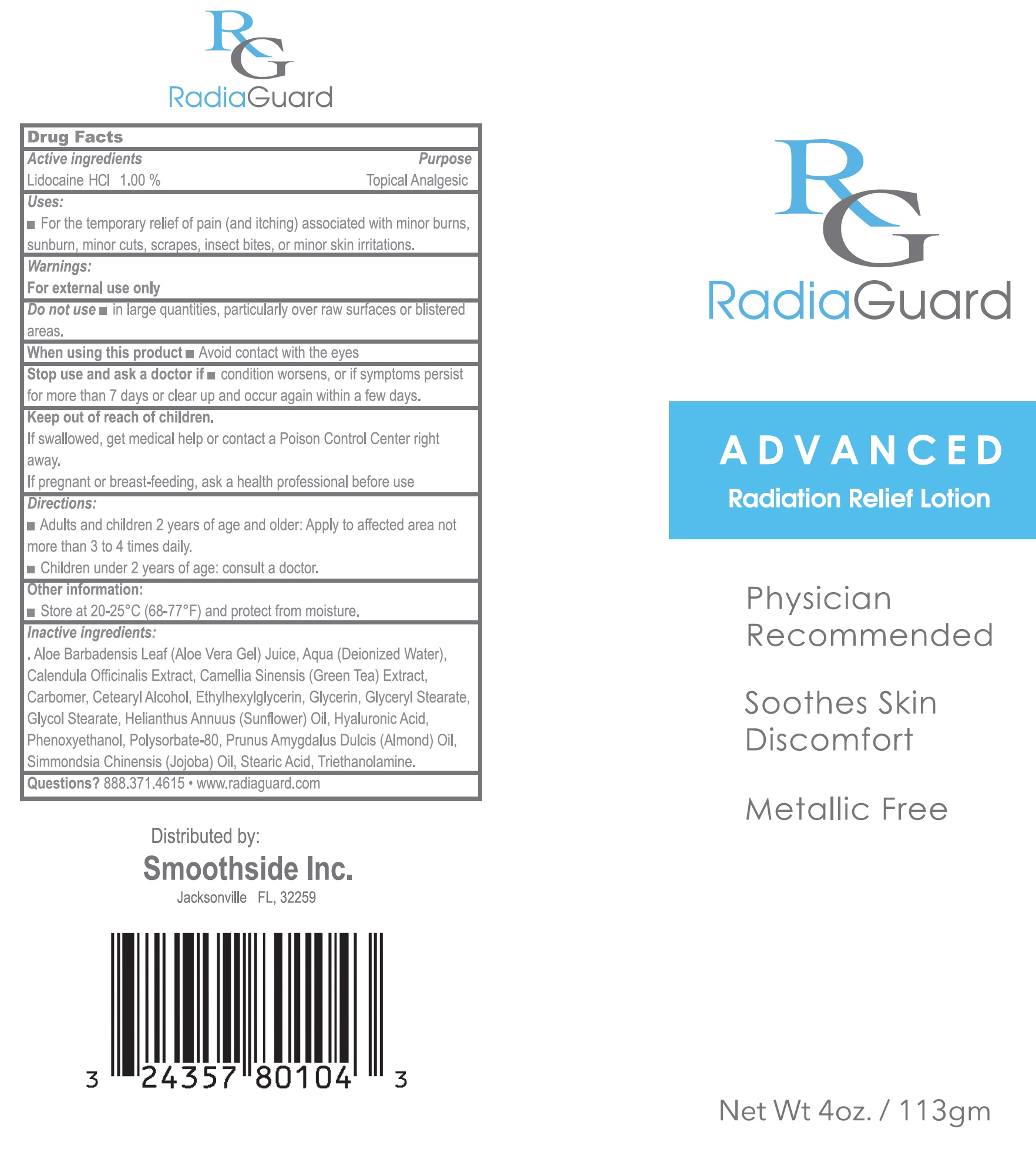 DRUG LABEL: RadiaGuard Advanced Radiation Relief
NDC: 81034-103 | Form: LOTION
Manufacturer: SMOOTH SIDE, INC
Category: otc | Type: HUMAN OTC DRUG LABEL
Date: 20231106

ACTIVE INGREDIENTS: LIDOCAINE HYDROCHLORIDE 10 mg/1 g
INACTIVE INGREDIENTS: ALOE VERA LEAF; WATER; CALENDULA OFFICINALIS FLOWER; GREEN TEA LEAF; CARBOMER HOMOPOLYMER, UNSPECIFIED TYPE; CETYL ALCOHOL; ETHYLHEXYLGLYCERIN; GLYCERIN; GLYCERYL MONOSTEARATE; GLYCOL STEARATE; SUNFLOWER OIL; HYALURONIC ACID; PHENOXYETHANOL; POLYSORBATE 80; ALMOND OIL; JOJOBA OIL; STEARIC ACID; TROLAMINE

RadiaGuard Advanced Radiation Relief Lotion

Active ingredients

Lidocaine HCl 1.00%

Purpose

Topical Analgesic

Uses:

- For the temporary relief of pain (and itching) associated with minor burns, sunburns, minor cuts, scrapes, insect bites, or minor skin irritations.

Warnings

For external use only.

Do not use

- in large quantities, particularly over raw surfaces or blistered areas.

When using this product

Avoid contact with the eyes

Stop use and ask a doctor if

- condition worsens, or if symptoms persist for more than 7 days or clear up and occur again within a few days.

Keep out of reach of children.

If swallowed, get medical help or contact a Poison Control Center right away.

If pregnant or breast-feeding,

ask a health professional before use

Directions

- Adults and children 2 years of age and older: Apply to affected area not more than 3 to 4 times daily.
- Children under 2 years of age: consult a doctor.

Other inforamtion:

- Store at 20-25°C (68-77°F) and protect from moisture.

Inactive ingredients:

Aloe Barbadensis Leaf (Aloe Vera Gel) Juice, Aqua (Deionized Water), Calendula Officinals Extract, Camellia Sineisis (Green Tea) Extract, Carbomer, Cetyl Alcohol, Ethylhexylglyerin, Glycerin, Glyceryl Stearate, Glycol Stearate, Helianthus Annuus (Sunflower) Oil, Hyaluronic Acid, Phenoxyethanol, Polysorbate-80, Prunus Amygdalus Dulcis (Almond) Oil, Simmondsia Chinesis (Jojoba) Oil, Stearic Acid, Triethanolamine.

Questions?

888.371.4615

- www.radiaguard.com